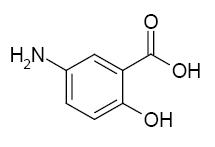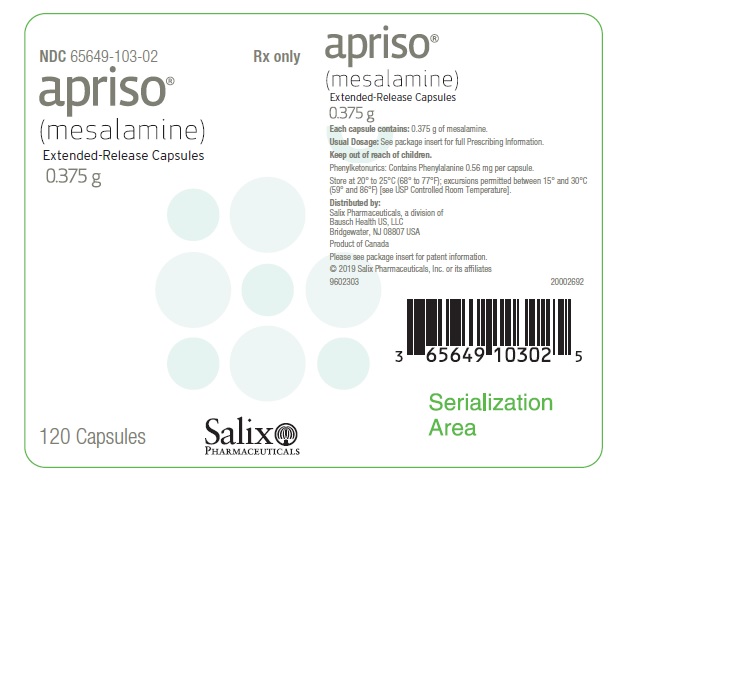 DRUG LABEL: APRISO
NDC: 65649-103 | Form: CAPSULE, EXTENDED RELEASE
Manufacturer: Salix Pharmaceuticals, Inc.
Category: prescription | Type: HUMAN PRESCRIPTION DRUG LABEL
Date: 20240109

ACTIVE INGREDIENTS: MESALAMINE 375 mg/1 1
INACTIVE INGREDIENTS: ANHYDROUS CITRIC ACID; CROSPOVIDONE; SILICON DIOXIDE; MAGNESIUM STEARATE; MICROCRYSTALLINE CELLULOSE; HYPROMELLOSE, UNSPECIFIED; METHACRYLIC ACID - METHYL METHACRYLATE COPOLYMER (1:1); TALC; TITANIUM DIOXIDE; TRIETHYL CITRATE; ASPARTAME

HIGHLIGHTS OF PRESCRIBING INFORMATION

These highlights do not include all the information needed to use APRISO safely and effectively. See full prescribing information for APRISO.
APRISO®(mesalamine) extended-release capsules
Initial U.S. Approval: 1987

1 INDICATIONS AND USAGE

APRISO is an aminosalicylate indicated for the maintenance of remission of ulcerative colitis in adults. (1)

2 DOSAGE AND ADMINISTRATION

Dosage
The recommended dosage is 1.5 g (four 0.375 g capsules) once daily in the morning. (2)

Administration Instructions

- Evaluate renal function before initiating therapy with APRISO. (2)
- Swallow the capsules whole. Do not cut, break, crush or chew the capsules. (2)
- Avoid co-administration with antacids. (2, 7.1)
- Drink an adequate amount of fluids. (2, 5.7)
- Take APRISO without regard to meals. (2)

3 DOSAGE FORMS AND STRENGTHS

Extended-release capsules: 0.375 g (3)

4 CONTRAINDICATIONS

Known or suspected hypersensitivity to salicylates, aminosalicylates, or any component of APRISO capsules. (4, 5.3)

5 WARNINGS AND PRECAUTIONS

- Renal Impairment:Assess renal function at the beginning of treatment and periodically during treatment. Evaluate the risks and benefits in patients with known renal impairment or taking nephrotoxic drugs; monitor renal function. Discontinue if renal function deteriorates. (5.1, 7.2, 8.6)
- Mesalamine-Induced Acute Intolerance Syndrome:Symptoms may be difficult to distinguish from an exacerbation of ulcerative colitis; monitor for worsening symptoms; discontinue treatment if acute intolerance syndrome is suspected. (5.2)
- Hypersensitivity Reactions, including Myocarditis and Pericarditis:Evaluate patients immediately and discontinue if a hypersensitivity reaction is suspected. (5.3)
- Hepatic Failure:Evaluate the risks and benefits in patients with known liver impairment. (5.4)
- Severe Cutaneous Adverse Reactions:Discontinue at the first signs or symptoms of severe cutaneous adverse reactions or other signs of hypersensitivity and consider further evaluation. (5.5)
- Photosensitivity: Advise patients with pre-existing skin conditions to avoid sun exposure, wear protective clothing, and use a broad-spectrum sunscreen when outdoors. (5.6)
- Nephrolithiasis:Mesalamine-containing stones are undetectable by standard radiography or computed tomography (CT). Ensure adequate fluid intake during treatment. (5.7)
- Risks in Patients with Phenylketonuria: Contains phenylalanine. Before prescribing APRISO to a patient with PKU, consider the combined daily amount of phenylalanine from all sources, including APRISO. (5.8)
- Interference with Laboratory Tests: Use of mesalamine may lead to spuriously elevated test results when measuring urinary normetanephrine by liquid chromatography with electrochemical detection. (5.9)

6 ADVERSE REACTIONS

Most common adverse reactions (≥3%) are: headache, diarrhea, upper abdominal pain, nausea, and nasopharyngitis. (6.1)

To report SUSPECTED ADVERSE REACTIONS, contact Salix Pharmaceuticals at 1-800-321-4576 or FDA at 1-800-FDA-1088 or www.fda.gov/medwatch.

7 DRUG INTERACTIONS

- Nephrotoxic Agents including NSAIDs:Increased risk of nephrotoxicity; monitor for changes in renal function and mesalamine-related adverse reactions. (7.2)
- Azathioprine or 6-Mercaptopurine:Increased risk of blood disorders; monitor complete blood cell counts and platelet counts. (7.3)

8 USE IN SPECIFIC POPULATIONS

Geriatric Patients: Increased risk of blood dyscrasias; monitor blood cell counts and platelet counts. (8.5)

FULL PRESCRIBING INFORMATION

1 INDICATIONS AND USAGE

APRISO®is indicated for the maintenance of remission of ulcerative colitis in adults.

2 DOSAGE AND ADMINISTRATION

Dosage
The recommended dosage in adults is 1.5 g (four 0.375 g capsules) orally once daily in the morning.

Administration Instructions

- Evaluate renal function before initiating therapy with APRISO [see Warnings and Precautions (5.1)].
- Swallow APRISO capsules whole. Do not cut, break, crush or chew the capsules.
- Avoid co-administration of APRISO with antacids [see Drug Interactions (7.1)].
- Drink an adequate amount of fluids [see Warnings and Precautions (5.7)].
- Take APRISO without regard to meals [see Clinical Pharmacology (12.3)].

3 DOSAGE FORMS AND STRENGTHS

Extended-release capsules: 0.375 g mesalamine in a light blue opaque gelatin capsule with the letters “G” and “M” imprinted on either side of a black band.

4 CONTRAINDICATIONS

APRISO is contraindicated in patients with hypersensitivity to salicylates or aminosalicylates or to any of the components of APRISO capsules [see Warnings and Precautions (5.3), Adverse Reactions (6.2), Description (11)] .

5 WARNINGS AND PRECAUTIONS

5.1 Renal Impairment

Renal impairment, including minimal change disease, acute and chronic interstitial nephritis, and renal failure, has been reported in patients given products such as APRISO that contain mesalamine or are converted to mesalamine. In animal studies, the kidney was the principal organ of mesalamine toxicity [see Adverse Reactions (6.2), Nonclinical Toxicology (13.2)].

Evaluate renal function prior to initiation of APRISO therapy and periodically while on therapy. Evaluate the risks and benefits of using APRISO in patients with known renal impairment or a history of renal disease or taking concomitant nephrotoxic drugs. Discontinue APRISO if renal function deteriorates while on therapy [see Drug Interactions (7.2), Use in Specific Populations (8.6)] .

5.2 Mesalamine-Induced Acute Intolerance Syndrome

Mesalamine has been associated with an acute intolerance syndrome that may be difficult to distinguish from an exacerbation of ulcerative colitis. Although the exact frequency of occurrence has not been determined, it has occurred in 3% of patients in controlled clinical trials of mesalamine or sulfasalazine. Symptoms include cramping, acute abdominal pain and bloody diarrhea, sometimes fever, headache, and rash. Monitor patients for worsening of these symptoms while on treatment. If acute intolerance syndrome is suspected, promptly discontinue treatment with APRISO.

5.3 Hypersensitivity Reactions

Some patients have experienced a hypersensitivity reaction to sulfasalazine. Some patients may have a similar reaction to APRISO or to other compounds that contain or are converted to mesalamine.

As with sulfasalazine, mesalamine-induced hypersensitivity reactions may present as internal organ involvement, including myocarditis, pericarditis, nephritis, hepatitis, pneumonitis and hematologic abnormalities. Evaluate patients immediately if signs or symptoms of a hypersensitivity reaction are present. Discontinue APRISO if an alternative etiology for the signs and symptoms cannot be established.

5.4 Hepatic Failure

There have been reports of hepatic failure in patients with pre-existing liver disease who have been administered mesalamine. Evaluate the risks and benefits of using APRISO in patients with known liver impairment.

5.5 Severe Cutaneous Adverse Reactions

Severe cutaneous adverse reactions, including Stevens-Johnson syndrome (SJS) and toxic epidermal necrolysis (TEN), drug reaction with eosinophilia and systemic symptoms (DRESS), and acute generalized exanthematous pustulosis (AGEP) have been reported with the use of mesalamine [see Adverse Reactions (6.2)] . Discontinue APRISO at the first signs or symptoms of severe cutaneous adverse reactions or other signs of hypersensitivity and consider further evaluation.

5.6 Photosensitivity

Patients with pre-existing skin conditions such as atopic dermatitis and atopic eczema have reported more severe photosensitivity reactions. Advise patients to avoid sun exposure, wear protective clothing, and use a broad-spectrum sunscreen when outdoors.

5.7 Nephrolithiasis

Cases of nephrolithiasis have been reported with the use of mesalamine, including stones with 100% mesalamine content. Mesalamine-containing stones are radiotransparent and undetectable by standard radiography or computed tomography (CT). Ensure adequate fluid intake during treatment with APRISO.

5.8 Risks in Patients with Phenylketonuria

Phenylalanine can be harmful to patients with phenylketonuria (PKU). APRISO contains phenylalanine, a component of aspartame. Each APRISO 0.375 g capsule contains 0.56 mg of phenylalanine. Before prescribing APRISO to a patient with PKU, consider the combined daily amount of phenylalanine from all sources, including APRISO.

5.9 Interference with Laboratory Tests

Use of APRISO may lead to spuriously elevated test results when measuring urinary normetanephrine by liquid chromatography with electrochemical detection because of the similarity in the chromatograms of normetanephrine and the main metabolite of mesalamine, N-acetyl-5-aminosalicylic acid (N-Ac-5-ASA). Consider an alternative, selective assay for normetanephrine.

6 ADVERSE REACTIONS

The following clinically significant adverse reactions are described elsewhere in labeling:

- Renal Impairment [see Warnings and Precautions (5.1)]
- Mesalamine-Induced Acute Intolerance Syndrome [see Warnings and Precautions (5.2)]
- Hypersensitivity Reactions [see Warnings and Precautions (5.3)]
- Hepatic Failure [see Warnings and Precautions (5.4)]
- Severe Cutaneous Adverse Reactions [see Warnings and Precautions (5.5)]
- Photosensitivity [see Warnings and Precautions (5.6)]
- Nephrolithiasis [see Warnings and Precautions (5.7)]
- Risks in Patients with Phenylketonuria [see Warnings and Precautions (5.8)]

6.1 Clinical Trials Experience

Because clinical studies are conducted under widely varying conditions, adverse reaction rates observed in the clinical trials of a drug cannot be directly compared to rates in the clinical trials of another drug and may not reflect the rates observed in practice.

The data described below reflect exposure to APRISO in 557 patients, including 354 exposed for at least 6 months and 250 exposed for greater than one year. APRISO was studied in two placebo-controlled trials (n=367 treated with APRISO) and in one open-label, long-term study (n=190 additional patients). The population consisted of patients with ulcerative colitis; the mean age was 47 years, 54% were female, and 93% were white. Patients received doses of APRISO 1.5 g administered orally once per day for six months in the placebo-controlled trials and for up to 24 months in the open‑label study.

In the two placebo-controlled trials, the most common reactions reported in at least 3% of APRISO-treated patients and at a greater rate than placebo are shown in Table 1 below.

Table 1: Common Adverse Reactions [Reported in at least 3% of APRISO-treated patients and at a greater rate than with placebo] in Clinical Trials of Adults with Ulcerative Colitis
 | APRISO 1.5 g once daily N=367 | Placebo N=185
Headache | 11% | 8%
Diarrhea | 8% | 7%
Upper Abdominal Pain | 5% | 3%
Nausea | 4% | 3%
Nasopharyngitis | 4% | 3%

The following adverse reactions, presented by body system, were reported at a frequency less than 3% in patients treated with APRISO for up to 24 months in controlled and open-label trials.

Ear and Labyrinth Disorders: tinnitus, vertigo

Dermatological Disorder: alopecia

Gastrointestinal: lower abdominal pain, rectal hemorrhage

Laboratory Abnormalities: increased triglycerides, decreased hematocrit and hemoglobin

General Disorders and Administration Site Disorders: fatigue

Hepatic: hepatitis cholestatic, transaminases increased

Renal Disorders: creatinine clearance decreased, hematuria

Musculoskeletal: pain, arthralgia

Respiratory: dyspnea

6.2 Postmarketing Experience

The following adverse reactions have been identified during post approval use of APRISO or other mesalamine-containing products. Because many of these reactions are reported voluntarily from a population of unknown size, it is not always possible to reliably estimate their frequency or establish a causal relationship to drug exposure.

Body as a Whole: lupus-like syndrome, drug fever

Cardiovascular: pericarditis, pericardial effusion, myocarditis [see Warnings and Precautions (5.3)]

Gastrointestinal: pancreatitis, cholecystitis, gastritis, gastroenteritis, gastrointestinal bleeding, perforated peptic ulcer

Hepatic: jaundice, cholestatic jaundice, hepatitis, liver necrosis, liver failure, Kawasaki-like syndrome including changes in liver enzymes

Hematologic: agranulocytosis, aplastic anemia

Nervous System: intracranial hypertension

Neurological/Psychiatric: peripheral neuropathy, Guillain-Barré syndrome, transverse myelitis

Renal and Urinary: nephrogenic diabetes insipidus, interstitial nephritis, renal failure, minimal change disease, nephrolithiasis [see Warnings and Precautions (5.1, 5.7)]

- Urine discoloration occurring ex-vivo caused by contact of mesalamine, including inactive metabolite, with surfaces or water treated with hypochlorite-containing bleach.

Respiratory/Pulmonary: eosinophilic pneumonia, interstitial pneumonitis, pleurisy/pleuritis

Skin: psoriasis, pyoderma gangrenosum, erythema nodosum, SJS/TEN, DRESS, and AGEP [ see Warnings and Precautions (5.5)]

Renal/Urogenital: reversible oligospermia

7 DRUG INTERACTIONS

7.1 Antacids

Because the dissolution of the coating of the granules in APRISO capsules depends on pH, avoid co-administration of APRISO capsules with antacids [see Dosage and Administration (2)] .

7.2 Nephrotoxic Agents, Including Non-Steroidal Anti-Inflammatory Drugs

The concurrent use of mesalamine with known nephrotoxic agents, including non-steroidal anti-inflammatory drugs (NSAIDs) may increase the risk of nephrotoxicity. Monitor patients taking nephrotoxic drugs for changes in renal function and mesalamine-related adverse reactions [see Warnings and Precautions (5.1)].

7.3 Azathioprine or 6-Mercaptopurine

The concurrent use of mesalamine with azathioprine or 6-mercaptopurine and/or other drugs known to cause myelotoxicity may increase the risk for blood disorders, bone marrow failure, and associated complications. If concomitant use of APRISO and azathioprine or 6-mercaptopurine cannot be avoided, monitor blood tests, including complete blood cell counts and platelet counts.

7.4 Interference with Urinary Normetanephrine Measurements

Use of APRISO may lead to spuriously elevated test results when measuring urinary normetanephrine by liquid chromatography with electrochemical detection [see Warnings and Precautions (5.9)] . Consider an alternative, selective assay for normetanephrine.

8 USE IN SPECIFIC POPULATIONS

8.1 Pregnancy

Risk Summary

Published data from meta-analyses, cohort studies and case series on the use of mesalamine during pregnancy have not reliably informed an association with mesalamine and major birth defects, miscarriage, or adverse maternal or fetal outcomes (see Data) .

In animal reproduction studies, there were no adverse developmental outcomes with administration of oral mesalamine during organogenesis to pregnant rats and rabbits at doses 1.7 and 5.4 times, respectively, the maximum recommended human dose (see Data) .

The estimated background risk of major birth defects and miscarriage for the indicated populations is unknown. Adverse outcomes in pregnancy occur regardless of the health of the mother or the use of medications. In the U.S. general population, the estimated background risk of major birth defects and miscarriage in clinically recognized pregnancies is 2 to 4% and 15 to 20%, respectively.

Clinical Considerations

Disease-associated maternal and embryo/fetal risk

Published data suggest that increased disease activity is associated with the risk of developing adverse pregnancy outcomes in women with ulcerative colitis. Adverse pregnancy outcomes include preterm delivery (before 37 weeks of

gestation), low birth weight (less than 2500 g) infants, and small for gestational age at birth.

Data

Human Data

Published data from meta-analyses, cohort studies and case series on the use of mesalamine during early pregnancy (first trimester) and throughout pregnancy have not reliably informed an association of mesalamine and major birth defects,

miscarriage, or adverse maternal or fetal outcomes. There is no clear evidence that mesalamine exposure in early pregnancy is associated with an increased risk in major congenital malformations, including cardiac malformations. Published epidemiologic studies have important methodological limitations which hinder interpretation of the data, including inability to control for confounders, such as underlying maternal disease, and maternal use of concomitant medications, and missing information on the dose and duration of use for mesalamine products.

Animal Data

Reproduction studies with mesalamine during organogenesis have been performed in rats at oral doses up to 320 mg/kg/day (about 1.7 times the recommended human dose based on a body surface area comparison) and rabbits at doses up to 495 mg/kg/day (about 5.4 times the recommended human dose based on a body surface area comparison) and have revealed no evidence of harm to the fetus due to mesalamine.

8.2 Lactation

Risk Summary

Data from published literature report the presence of mesalamine and its metabolite, N-acetyl 5-aminosalicylic acid in human milk in small amounts with relative infant doses (RID) of 2% or less (see Data) . There are case reports of diarrhea in breastfed infants exposed to mesalamine (see Clinical Considerations). There is no information on the effects of the drug on milk production. The lack of clinical data during lactation precludes a clear determination of the risk of APRISO to an infant during lactation; therefore, the developmental and health benefits of breastfeeding should be considered along with the mother’s clinical need for APRISO and any potential adverse effects on the breastfed child from APRISO or from the underlying maternal condition.

Clinical Considerations

Advise the caregiver to monitor the breastfed infant for diarrhea.

Data

In published lactation studies, maternal mesalamine doses from various oral and rectal formulations and products ranged from 500 mg to 4.8 g daily. The average concentration of mesalamine in milk ranged from non-detectable to 0.5 mg/L. The average concentration of the N-acetyl-5-aminosalicylic acid in milk ranged from 0.2 to 9.3 mg/L. Based on these concentrations, estimated infant daily dosages for an exclusively breastfed infant are 0 to 0.075 mg/kg/day (RID 0 to 0.1%) of mesalamine and 0.03 to 1.4 mg/kg/day of N-acetyl-5-aminosalicylic acid.

8.4 Pediatric Use

Safety and effectiveness of APRISO in pediatric patients have not been established.

8.5 Geriatric Use

Clinical studies of APRISO did not include sufficient numbers of subjects aged 65 years and older to determine whether they respond differently than younger subjects. Reports from uncontrolled clinical studies and postmarketing reporting systems suggested a higher incidence of blood dyscrasias (i.e., agranulocytosis, neutropenia and pancytopenia) in patients

who were 65 years or older compared to younger patients taking mesalamine-containing products such as APRISO. Monitor complete blood cell counts and platelet counts in elderly patients during treatment with APRISO. In general, consider the greater frequency of decreased hepatic, renal, or cardiac function, and of concomitant disease or other drug therapy in elderly patients when prescribing APRISO [see Use in Specific Populations (8.6)].

8.6 Renal Impairment

Mesalamine is known to be substantially excreted by the kidney, and the risk of adverse reactions to this drug may be greater in patients with impaired renal function. Evaluate renal function in all patients prior to initiation and periodically while on APRISO therapy. Monitor patients with known renal impairment or history of renal disease or taking nephrotoxic drugs for decreased renal function and mesalamine-related adverse reactions. Discontinue APRISO if renal function deteriorates while on therapy [see Warnings and Precautions (5.1), Adverse Reactions (6.2), Drug Interactions (7.2)].

10 OVERDOSAGE

APRISO is an aminosalicylate, and symptoms of salicylate toxicity include nausea, vomiting and abdominal pain, tachypnea, hyperpnea, tinnitus, and neurologic symptoms (headache, dizziness, confusion, seizures). Severe salicylate intoxication may lead to electrolyte and blood pH imbalance and potentially to other organ (e.g., renal and liver) damage. There is no specific antidote for mesalamine overdose; however, conventional therapy for salicylate toxicity may be beneficial in the event of acute overdosage and may include gastrointestinal tract decontamination to prevent further absorption. Correct fluid and electrolyte imbalance by the administration of appropriate intravenous therapy and maintain adequate renal function. APRISO is a pH-dependent delayed-release product and this factor should be considered when treating a suspected overdose.

11 DESCRIPTION

Each APRISO®capsule is a delayed- and extended-release dosage form for oral administration. Each capsule contains 0.375 g of mesalamine USP (5-aminosalicylic acid, 5-ASA), an aminosalicylate. The structural formula of mesalamine is:

Molecular Weight: 153.14

Molecular Formula: C7H7NO3

Each APRISO capsule contains granules composed of mesalamine in a polymer matrix with an enteric coating that dissolves at pH 6 and above.

The inactive ingredients of APRISO capsules are: anhydrous citric acid, aspartame, colloidal silicon dioxide, edible black ink, hypromellose, magnesium stearate, methacrylic acid copolymer, microcrystalline cellulose, povidone, simethicone emulsion, ethyl acrylate/methyl methacrylate copolymer, talc, titanium dioxide, triethyl citrate, vanilla flavor.

Each APRISO 0.375 g capsule contains 0.56 mg of phenylalanine.

12 CLINICAL PHARMACOLOGY

12.1 Mechanism of Action

The mechanism of action of mesalamine (5-ASA) is not fully understood, but appears to be a local anti-inflammatory effect on colonic epithelial cells. Mucosal production of arachidonic acid metabolites, both through the cyclooxygenase pathways, i.e., prostanoids, and through the lipoxygenase pathways, i.e., leukotrienes and hydroxyeicosatetraenoic acids, is increased in patients with ulcerative colitis, and it is possible that 5-ASA diminishes inflammation by blocking production of arachidonic acid metabolites.

12.3 Pharmacokinetics

Absorption

The pharmacokinetics of 5-ASA and its metabolite, N-acetyl-5-aminosalicylic acid (N-Ac-5-ASA), were studied after a single and multiple oral doses of 1.5 g APRISO in a crossover study in healthy subjects under fasting conditions. In the multiple-dose period, each subject received APRISO 1.5 g (four 0.375 g capsules) once daily for 7 consecutive days. Steady state was reached on Day 6 of once daily dosing based on trough concentrations.

After single and multiple doses of APRISO, peak plasma concentrations were observed at about 4 hours post-dose. At steady state, moderate increases (1.5-fold and 1.7-fold) in systemic exposure (AUC0-24) to 5-ASA and N-Ac-5-ASA were observed when compared with a single-dose of APRISO.

Pharmacokinetic parameters after a single dose of 1.5 g APRISO and at steady state in healthy subjects under fasting condition are shown in Table 2.

Table 2: Single Dose and Multiple Dose Mean (±SD) Plasma Pharmacokinetic Parameters of Mesalamine (5-ASA) and N-Ac-5-ASA After 1.5 g APRISO Administration in Healthy Subjects
Mesalamine (5-ASA) | Single Dose (n=24) | Multiple Dosec (n=24)
AUC0-24(mcg*h/mL) | 11±5 | 17±6
AUC0-inf(mcg*h/mL) | 14±5 | -
Cmax(mcg/mL) | 2.1±1.1 | 2.7±1.1
Tmax(h)a | 4 (2, 16) | 4 (2, 8)
t½(h)b | 9±7 | 10±8
N-Ac-5-ASA
AUC0-24(mcg*h/mL) | 26±6 | 37±9
AUC0-inf(mcg*h/mL) | 51±23 | -
Cmax(mcg/mL) | 2.8±0.8 | 3.4±0.9
Tmax(h)a | 4 (4, 12) | 5 (2, 8)
t½(h)b | 12±11 | 14±10
aMedian (range);bHarmonic mean (pseudo SD);cafter 7 days of treatment

In a separate study (n=30), it was observed that under fasting conditions about 32%±11% (mean±SD) of the administered dose was systemically absorbed based on the combined cumulative urinary excretion of 5-ASA and N-Ac-5-ASA over 96 hours post-dose.

Food Effects

The effect of a high fat meal intake on absorption of mesalamine granules (the same granules contained in APRISO capsules) was evaluated in 30 healthy subjects. Subjects received 1.6 g of mesalamine granules in sachet (2 x 0.8 g) following an overnight fast or a high fat meal in a crossover study. Under fed conditions, Tmaxfor both 5-ASA and N‑Ac‑5-ASA was prolonged by 4 and 2 hours, respectively. A high fat meal did not affect Cmaxfor 5-ASA, but a 27% increase in the cumulative urinary excretion of 5-ASA was observed with a high fat meal. The overall extent of absorption of N‑Ac-5-ASA was not affected by a high fat meal [see Dosage and Administration (2)] .

Distribution

In an in vitro study, at 2.5 mcg/mL, mesalamine and N-Ac-5-ASA are 43±6% and 78±1% bound, respectively, to plasma proteins. Protein binding of N-Ac-5-ASA does not appear to be concentration dependent at concentrations ranging from 1 to 10 mcg/mL.

Elimination

Metabolism

The major metabolite of mesalamine is N-acetyl-5-aminosalicylic acid (N-Ac-5-ASA). It is formed by N-acetyltransferase activity in the liver and intestinal mucosa.

Excretion

Following single and multiple doses of APRISO, the mean half-lives were 9 to 10 hours for 5-ASA, and 12 to 14 hours for N-Ac-5-ASA. Of the approximately 32% of the dose absorbed, about 2% of the dose was excreted unchanged in the urine, compared with about 30% of the dose excreted as N-Ac-5-ASA.

Drug Interaction Studies

In an in vitro study using human liver microsomes, 5-ASA and its metabolite, N-Ac-5-ASA, were shown not to inhibit the major CYP enzymes evaluated (CYP1A2, CYP2C9, CYP2C19, CYP2D6, and CYP3A4). Therefore, mesalamine and its metabolite are not expected to inhibit the metabolism of other drugs that are substrates of CYP1A2, CYP2C9, CYP2C19, CYP2D6, or CYP3A4.

13 NONCLINICAL TOXICOLOGY

13.1 Carcinogenesis, Mutagenesis, Impairment of Fertility

Dietary mesalamine was not carcinogenic in rats at doses as high as 480 mg/kg/day, or in mice at 2,000 mg/kg/day. These doses are about 2.6 and 5.4 times the recommended human dose of granulated mesalamine capsules of 1.5 g/day (30 mg/kg if 50 kg body weight assumed or 1,110 mg/m^2), respectively, based on body surface area.

Mesalamine was negative in the Ames test, the mouse lymphoma cell (L5178Y/TK+/-) forward mutation test, the sister chromatid exchange assay in the Chinese hamster bone marrow test, and the mouse bone marrow micronucleus test.

No effects on fertility or reproductive performance in male and female rats were observed with oral mesalamine doses up to 320 mg/kg (about 1.7 times the recommended human dose based on body surface area).

13.2 Animal Toxicology and/or Pharmacology

Renal Toxicity

Animal studies with mesalamine (13-week and 26-week oral toxicity studies in rats, and 26-week and 52-week oral toxicity studies in dogs) have shown the kidney to be the major target organ of mesalamine toxicity. Single oral doses of 800 mg/kg (about 2.2 times the recommended human dose, on the basis of body surface area) and 1,800 mg/kg (about 9.7 times the recommended human dose, on the basis of body surface area) of mesalamine were lethal to mice and rats, respectively, and resulted in gastrointestinal and renal toxicity. Oral doses of 40 mg/kg/day (about 0.20 times the human dose, on the basis of body surface area) produced minimal to slight tubular injury, and doses of 160 mg/kg/day (about 0.90 times the human dose, on the basis of body surface area) or higher in rats produced renal lesions including tubular degeneration, tubular mineralization, and papillary necrosis. Oral doses of 60 mg/kg/day (about 1.1 times the human dose, on the basis of body surface area) or higher in dogs also produced renal lesions including tubular atrophy, interstitial cell infiltration, chronic nephritis, and papillary necrosis.

14 CLINICAL STUDIES

Two similar, randomized, double-blind, placebo-controlled, multi-center studies were conducted in a total of 562 adult patients in remission from ulcerative colitis. The study populations had a mean age of 46 years (11% age 65 years or older), were 53% female, and were primarily white (92%).

Ulcerative colitis disease activity was assessed using a modified Sutherland Disease Activity Index (DAI), which is a sum of four subscores based on stool frequency, rectal bleeding, mucosal appearance on endoscopy, and physician’s rating of disease activity. Each subscore can range from 0 to 3, for a total possible DAI score of 12.

At baseline, approximately 80% of patients had a total DAI score of 0 or 1.0. Patients were randomized 2:1 to receive either APRISO 1.5 g or placebo once daily in the morning for six months. Patients were assessed at baseline, 1 month, 3 months, and 6 months in the clinic, with endoscopy performed at baseline, at end of study, or if clinical symptoms developed. Relapse was defined as a rectal bleeding subscale score of 1 or more and a mucosal appearance subscale score of 2 or more using the DAI. The analysis of the intent-to-treat population was a comparison of the proportions of patients who remained relapse-free at the end of six months of treatment. For the table below (Table 3) all patients who prematurely withdrew from the study for any reason were counted as relapses.

In both studies, the proportion of patients who remained relapse-free at six months was greater for APRISO than for placebo.

Table 3: Percentage of Ulcerative Colitis Patients Relapse-Free [Relapse counted as rectal bleeding score ≥1 and mucosal appearance score ≥2, or premature withdrawal from study.] Through 6 Months in APRISO Maintenance Studies
 | APRISO 1.5 g once daily % (# no relapse/N) | Placebo % (# no relapse/N) | Difference (95% C.I.) | P-value
Study 1 | 68% (143/209) | 51% (49/96) | 17% (5.5, 29.2) | <0.001
Study 2 | 71% (117/164) | 59% (55/93) | 12% (0, 24.5) | 0.046

Examination of gender subgroups did not identify difference in response to APRISO among these subgroups. There were too few elderly and too few African-American patients to adequately assess difference in effects in those populations.

The use of APRISO for treating ulcerative colitis beyond six months has not been evaluated in controlled clinical trials.

16 HOW SUPPLIED/STORAGE AND HANDLING

APRISO®extended-release capsules are available as light blue opaque hard gelatin capsules containing 0.375 g mesalamine in a light blue opaque gelatin capsule with the letters “G” and “M” imprinted on either side of a black band and are available in bottles of 120 capsules (NDC 65649-103-02).

Storage:

Store at 20° to 25°C (68° to 77°F); excursions permitted between 15° and 30°C (59° and 86°F) [see USP Controlled Room Temperature].

17 PATIENT COUNSELING INFORMATION

Administration

Instruct patients:

- Swallow the capsules whole. Do not cut, break, crush or chew the capsules.
- Avoid co-administration of APRISO with antacids.
- Drink an adequate amount of fluids.
- APRISO capsules can be taken without regard to meals [ see Dosage and Administration (2)] .
- Urine may become discolored reddish-brown while taking APRISO when it comes in contact with surfaces or water treated with hypochlorite-containing bleach. If discolored urine is observed, advise patients to observe their urine flow. Report to the healthcare provider only if urine is discolored on leaving the body, before contact with any surface or water (e.g., in the toilet).

Renal Impairment

Inform patients that APRISO may decrease their renal function, especially if they have known renal impairment or are taking nephrotoxic drugs, including NSAIDs, and periodic monitoring of renal function will be performed while they are on therapy. Advise patients to complete all blood tests ordered by their healthcare provider [ see Warnings and Precautions (5.1), Drug Interactions (7.2)] .

Mesalamine-Induced Acute Intolerance Syndrome and Other Hypersensitivity Reactions

Inform patients of the signs and symptoms of hypersensitivity reactions. Instruct patients to stop taking APRISO and report to their healthcare provider if they experience new or worsening symptoms of Acute Intolerance Syndrome (cramping, abdominal pain, bloody diarrhea, fever, headache, and rash) or other symptoms suggestive of mesalamine-induced hypersensitivity [ see Warnings and Precautions (5.2, 5.3)] .

Hepatic Failure

Inform patients with known liver disease of the signs and symptoms of worsening liver function and advise them to report to their healthcare provider if they experience such signs or symptoms [ see Warnings and Precautions (5.4)] .

Severe Cutaneous Adverse Reactions

Inform patients of the signs and symptoms of severe cutaneous adverse reactions. Instruct patients to stop taking APRISO and report to their healthcare provider at first appearance of a severe cutaneous adverse reaction or other sign of hypersensitivity [ see Warnings and Precautions (5.5)].

Photosensitivity

Advise patients with pre-existing skin conditions to avoid sun exposure, wear protective clothing, and use a broad-spectrum sunscreen when outdoors [ see Warnings and Precautions (5.6)] .

Nephrolithiasis

Instruct patients to drink an adequate amount of fluids during treatment in order to minimize the risk of kidney stone formation and to contact their healthcare provider if they experience signs or symptoms of a kidney stone (e.g., severe side or back pain, blood in the urine) [ see Warnings and Precautions (5.7)] .

Patients with Phenylketonuria

Inform patients with phenylketonuria (PKU) or their caregivers that each APRISO capsule contains aspartame equivalent to 0.56 mg of phenylalanine, so that the recommended adult dosing provides an equivalent of 2.24 mg of phenylalanine per day [ see Warnings and Precautions (5.8)] .

Blood Disorders

Inform elderly patients and those taking azathioprine or 6-mercaptopurine of the risk for blood disorders and the need for periodic monitoring of complete blood cell counts and platelet counts while on therapy. Advise patients to complete all blood tests ordered by their healthcare provider [see Drug Interactions (7.3), Use in Specific Populations (8.5)] .

Distributed by:
Salix Pharmaceuticals, a division of
Bausch Health US, LLC
Bridgewater, NJ 08807 USA
Patented. See https://patents.salix.com/for US patent information.

APRISO is a trademark of Salix Pharmaceuticals, Inc. or its affiliates.

© 2023 Salix Pharmaceuticals, Inc. or its affiliates

9602407
20005431

PACKAGE/LABEL PRINCIPAL DISPLAY PANEL

NDC65649-103-02

Rx only

apriso®
(mesalamine)
Extended-Release Capsules
0.375 g

120 Capsules

Salix Pharmaceuticals